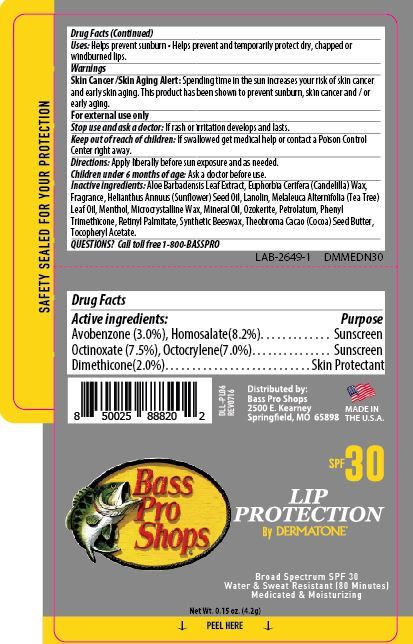 DRUG LABEL: Dermatone SPF 30 Bass Pro Shop
NDC: 54414-109 | Form: STICK
Manufacturer: Dermatone
Category: otc | Type: HUMAN OTC DRUG LABEL
Date: 20251216

ACTIVE INGREDIENTS: AVOBENZONE 30 mg/1 g; HOMOSALATE 82 mg/1 g; OCTINOXATE 75 mg/1 g; OCTOCRYLENE 50 mg/1 g; DIMETHICONE 100 400 mg/1 g
INACTIVE INGREDIENTS: LIGHT MINERAL OIL 122 mg/1 g; CERESIN 170 mg/1 g

Drug Facts

Active ingredient

Avobenzone 3.0%, Homosalate 8.2%, Octinoxate 7.5%, Octocrylenene7.0%................Sunscreen, Dimethicone 2.0.0%...........Skin Protectant

Purpose

Sunscreen, Skin Protectant

Keep Out of Reach of Children

If swallowed get medical help or contact a Poison Control Center right away.

Uses

Helps prevent sunburns. Helps prevent and temporarily protect dry, chapped or windburned lips.

Warnings

Skin Cancer/Skin Aging Alert: Spending time in the sun increases your risk of skin cancer and early skin aging. This product has been shown to prevent sunburn, skin cancer and/or early aging.

For external use only: Stop use and ask a doctor: if rash or irritation develops and lasts.

Directions

Apply liberally 15 minutes before sun exposure • reapply: after 80 minutes

of swimming or sweating • immediately after towel drying • at least every 2 hours • Sun

Protection Measures.Spending time in the sun increases your risk of skin cancer and

early skin aging • To decrease the risk, regularly use a sunscreen with a broad spectrum

SPF of 15 or higher and other sun protection measures including: limit time in the sun,

especially from 10 a.m. -2 p.m. • wear long-sleeve shirts, pants, hats and sunglasses. Children under 6 months: Ask a doctor.

Inactive Ingredients

Aloe Barbadensis Leaf Extract, Euphorbia Cerifera (Candellila) Wax, Fragrance, Helianthus Annuus (Sunflower) Seed Oil, Lanolin, Melaleuca Alternifolia (Tea Tree) Leaf Oil, Menthol, Microcrystalline Wax, Mineral Oil, Ozokerite, Petrolatum, Phenyl Trimethicone, Retinyl Palmitate, Synthetic Beeswax, Theobroma Cacao (Cocoa) Seed Butter, Tocopheryl Acetate.